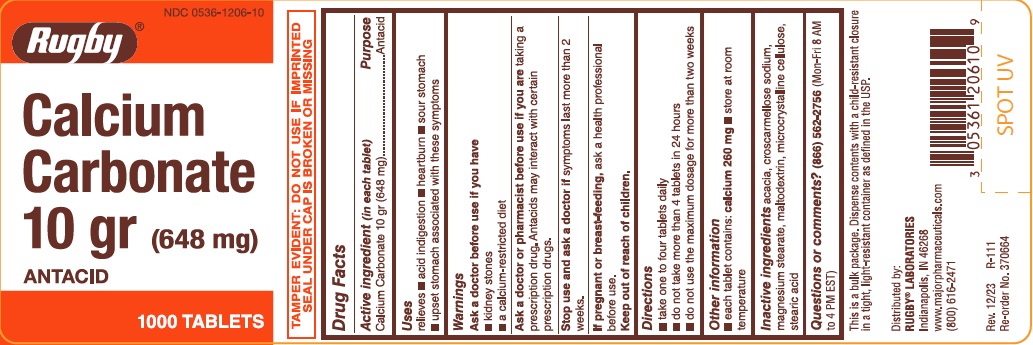 DRUG LABEL: Calcium Carbonate 10 gr (648 mg)
NDC: 0536-1206 | Form: TABLET
Manufacturer: RUGBY LABORATORIES
Category: otc | Type: HUMAN OTC DRUG LABEL
Date: 20241217

ACTIVE INGREDIENTS: CALCIUM CARBONATE 648 mg/1 1
INACTIVE INGREDIENTS: ACACIA; CROSCARMELLOSE SODIUM; MAGNESIUM STEARATE; MALTODEXTRIN; MICROCRYSTALLINE CELLULOSE; STEARIC ACID

Drug Facts

Active ingredient (in each tablet)

Calcium Carbonate 10 gr (648 mg)

Purpose

Antacid

Uses

relieves

- acid indigestion
- heartburn
- sour stomach
- upset stomach associated with these symptoms

Warnings

Ask a doctor before use if you have

- kidney stones
- a calcium-restricted diet

Ask a doctor or pharmacist before use if you are

taking a prescription drug. Antacids may interact with certain prescription drugs.

Stop use and ask a doctor if

symptoms last more than 2 weeks.

If pregnant or breast-feeding,

ask a health professional before use.

Directions

- take one to four tablets daily
- do not take more than 4 tablets in 24 hours
- do not use the maximum dosage for more than two weeks

Other information

- each tablet contains: calcium 260 mg
- store at room temperature

Inactive ingredients

acacia, croscarmellose sodium, magnesium stearate, maltodextrin, microcrystalline cellulose, stearic acid

Questions or comments?

(866) 562-2756 (Mon-Fri 8 AM to 4 PM EST)

TAMPER EVIDENT: DO NOT USE IF IMPRINTED SEAL UNDER CAP IS BROKEN OR MISSING

This is a bulk package. Dispense contents with a child-resistant closure in a tight, light-resistant container as defined in the USP.

PACKAGE LABEL

NDC 0536-1206-10

Rugby ®

Calcium

Carbonate

10 gr (648 mg)

ANTACID

1000 TABLETS